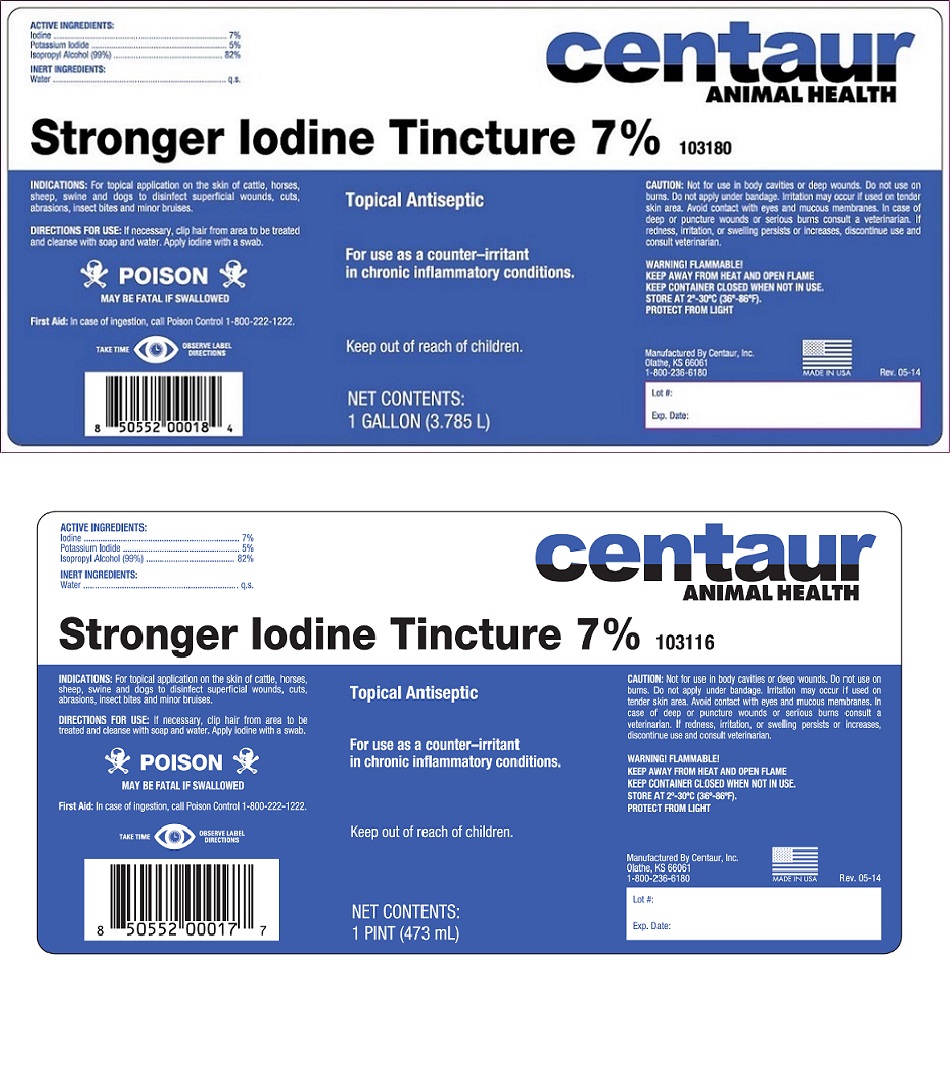 DRUG LABEL: Stronger Iodine Tincture
NDC: 58305-031 | Form: SOLUTION
Manufacturer: Centaur, Inc.
Category: animal | Type: OTC ANIMAL DRUG LABEL
Date: 20250221

ACTIVE INGREDIENTS: IODINE 70 mg/1 mL; POTASSIUM IODIDE 50 mg/1 mL; ISOPROPYL ALCOHOL 82 mg/1 mL

STRONGER IODINE TINCTURE 7%

DESCRIPTION

Topical Antiseptic

For use as a counter-irritant in chronic infammatory conditions.

Keep out of reach of children.

ACTIVE INGREDIENTS
Iodine............................................. 7%
Potassium Iodide.......................... 5%
Isopropyl Alcohol (99%)........... 82%

INERT INGREDIENTS
Water............................................. q.s.

INDICATIONS

For topical application on the skin of cattle, horses, sheep, swine and dogs to disinfect superficial wounds, cuts, abrasions, insect bites and minor bruises.

DIRECTIONS FOR USE

If necessary, clip hair from area to be treated and cleanse with soap and water. Apply iodine with a swab.

USER SAFETY WARNINGS

POISON

MAY BE FATAL IF SWALLOWED

First Aid: In case of ingestion, call Poison Control 1-800-222-1222

TAKE TIME OBSERVE LABEL DIRECTIONS

CAUTION

Not for use in body cavities or deep wounds. Do not use on burns. Do not apply under bandage. Irritation may occur if used on tender skin area. Avoid contact with eyes and mucus membrains. In case of deep or punture wounds or serious burns consult a veterinarian. If redness, irritation, or swelling persist or increases, discontinue use and consult veterinarian.

WARNINGS

WARNING FLAMMABLE

KEEP AWAY FROM HEAT AND OPEN FLAME.

KEEP CONTAINER CLOSED WHEN NOT IN USE.

STORAGE AND HANDLING

STORE AT 2o-30oC (36o-86o).

PROTECT FROM LIGHT.